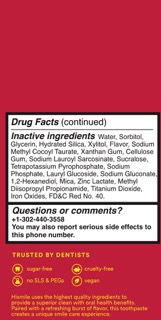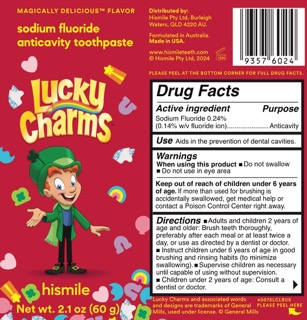 DRUG LABEL: Hismile
NDC: 83013-335 | Form: GEL, DENTIFRICE
Manufacturer: Hismile Pty Ltd
Category: otc | Type: HUMAN OTC DRUG LABEL
Date: 20250318

ACTIVE INGREDIENTS: SODIUM FLUORIDE 0.243 g/100 g
INACTIVE INGREDIENTS: WATER; SODIUM GLUCONATE; SODIUM LAURYL SARCOSINATE; 1,2-HEXANEDIOL; ZINC LACTATE; METHYL DIISOPROPYL PROPIONAMIDE; TITANIUM DIOXIDE; SUCRALOSE; LAURYL GLUCOSIDE; XYLITOL; XANTHAN GUM; SORBITOL; GLYCERIN; HYDRATED SILICA; IRON OXIDES; FD&C RED NO. 40; TETRAPOTASSIUM PYROPHOSPHATE; SODIUM PHOSPHATE; SODIUM METHYL COCOYL TAURATE; MICA; CELLULOSE GUM

Active ingredient

Sodium Fluoride 0.243%

(0.14 w/v fluoride ion)

Purpose

Anticavity

Use

Aids in the prevention of dental cavities

Warnings

When using this product

- Do not swallow
- Do not use in eye area

Keep out of reach of children under 6 years of age.

If more than used for brushing is accidentally swallowed, get medical help or contact a Poison Control Center right away.

Directions

Adults and children 2 years of age and older: Brush teeth thoroughly, preferably after each meal or at least twice a day, or use as directed by a dentist or doctor.

Instruct children under 6 years of age in good brushing and rinsing habits (to minimize swallowing).

Supervise children as necessary until capable of using without supervision.

Children under 2 years of age: Consult a dentist or doctor.

INACTIVE INGREDIENT

Water

Sorbitol

Glycerin

Hydrated Silica

Xylitol

Flavor

Sodium Methyl Cocoyl Taurate

Xanthan Gum

Cellulose Gum

Sodium Lauroyl Sarcosinate

Sucralose

Tetrapotassium Pyrophosphate

Sodium Phosphate

Lauryl Glucoside

Sodium Gluconate

1,2-Hexanediol

Mica

Zinc Lactate

Methyl Diisopropyl Propionamide

Titanium Dioxide

Iron Oxides

FD&C Red No.40

PACKAGE LABEL

Hismile Lucky Charms Magically Delicious Flavor Sodium Fluoride Anticavity Toothpaste Gel